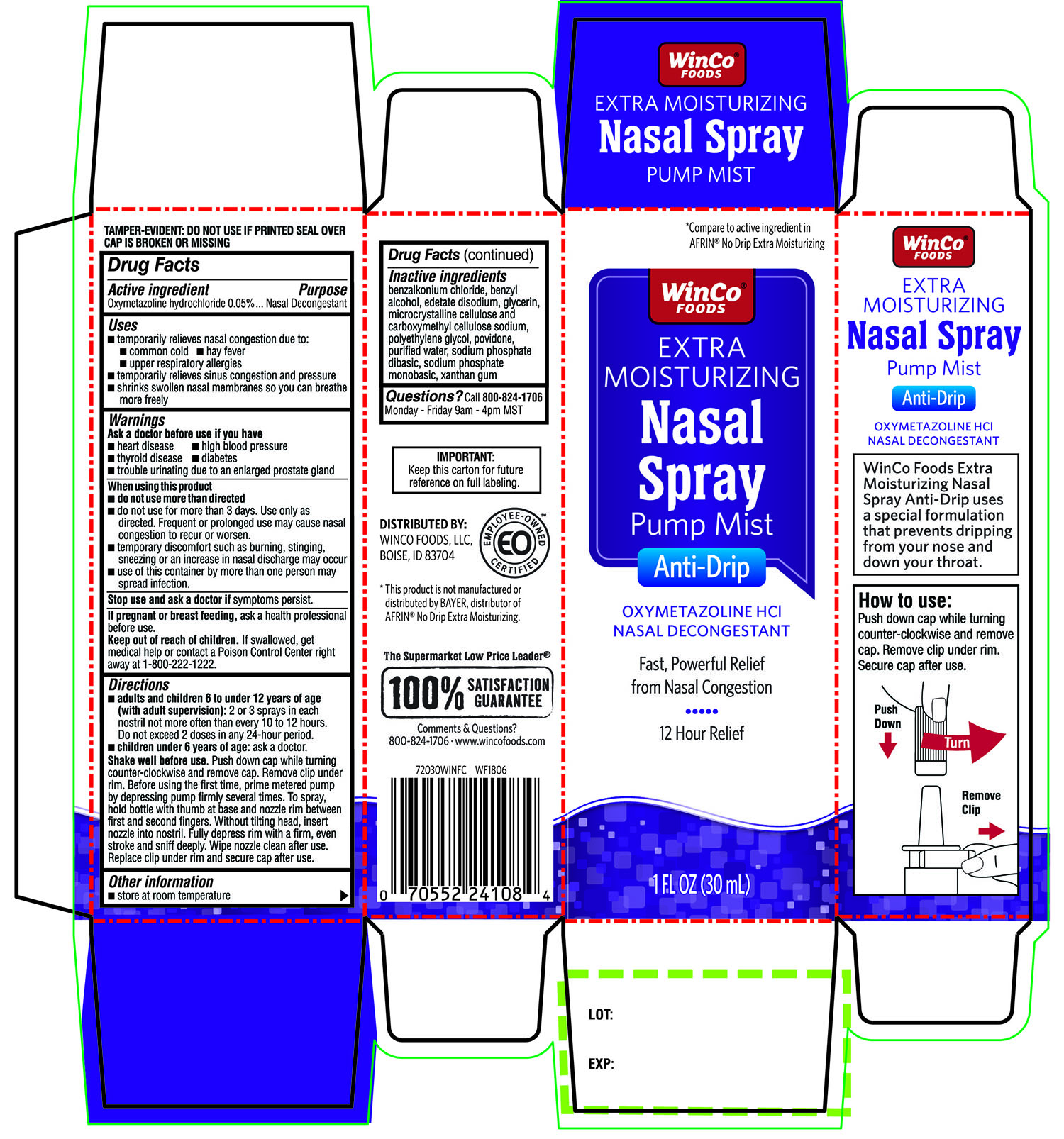 DRUG LABEL: Extra Moisturizing Nasal Pump Mist

NDC: 67091-324 | Form: SPRAY
Manufacturer: WinCo FOODS, LLC
Category: otc | Type: HUMAN OTC DRUG LABEL
Date: 20251202

ACTIVE INGREDIENTS: OXYMETAZOLINE HYDROCHLORIDE 0.05 g/100 mL
INACTIVE INGREDIENTS: BENZALKONIUM CHLORIDE; BENZYL ALCOHOL; EDETATE DISODIUM; GLYCERIN; MICROCRYSTALLINE CELLULOSE; CARBOXYMETHYLCELLULOSE SODIUM, UNSPECIFIED; POLYETHYLENE GLYCOL 400; POVIDONE K90; WATER; SODIUM PHOSPHATE, DIBASIC, ANHYDROUS; SODIUM PHOSPHATE, MONOBASIC, ANHYDROUS; XANTHAN GUM

WinCo®FOODS Extra Moisturizing Nasal Spray Pump Mist Anti-Drip OXYMETAZOLINE HCL NASAL DECONGESTANT 1FL OZ

Active ingredient

Oxymetazoline hydrochloride 0.05%

Purpose

Nasal Decongestant

Uses

- temporarily relieves nasal congestion due to:
- common cold
- hay fever
- upper respiratory allergies
- temporarily relieves sinus congestion and pressure
- shrinks swollen nasal membranes so you can breathe more freely

Warnings

Ask a doctor before use if you have

- heart disease
- high blood pressure
- thyroid disease
- diabetes
- trouble urinating due to an enlarged prostate gland

When using this product

- do not use more than directed
- do not use for more than 3 days. Use only as directed. Frequent or prolonged use may cause nasal congestion to recur or worsen.
- temporary discomfort such as burning, stinging, sneezing or an increase in nasal discharge may occur
- use of this container by more than one person may spread infection

Stop use and ask a doctor if

symptoms persist

If pregnant or breast-feeding,

ask a health professional before use.

Keep out of reach of children.

If swallowed, get medical help or contact a Poison Control Center right away at 1-800-222-1222.

Directions

- adults and children 6 to under 12 years of age (with adult supervision):2 or 3 sprays in each nostril not more often than every 10 to 12 hours. Do not exceed 2 doses in any 24-hour period.
- children under 6 years of age:ask a doctor.

Shake well before use. Push down cap while turning counter-clockwise and remove cap. Remove clip under rim. Before using the first time, prime metered pump by depressing pump firmly several times. To spray, hold bottle with thumb at base and nozzle rim between first and second fingers. Without tilting head, insert nozzle into nostril. Fully depress rim with a firm, even stroke and sniff deeply. Wipe nozzle clean after use. Replace clip under rim and secure cap after use.

Other information

- store at room temperature

Inactive ingredients

benzalkonium chloride, benzyl alcohol, edetate disodium, glycerin, microcrystalline cellulose and carboxymethyl cellulose sodium, polyethylene glycol, povidone, purified water, sodium phosphate dibasic, sodium phosphate monobasic, xanthan gum.

Questions?

Call 800-824-1706Monday-Friday 9 am-4pm MST

Principal Display Panel

NDC 67091-324-30

*Compare to Active Ingredient in AFRIN®No-Drip Extra Moisturizing

WinCo®FOODS EXTRA MOISTURIZING

Nasal Spray

Pump Mist

Anti-Drip

OXYMETAZOLINE HCL

NASAL DECONGESTANT

Fast, Powerful Relief from Nasal Congestion

12 Hour Relief

1 FL OZ (30 mL)

WinCo Foods Extra Moisturizing Nasal Spray Anti-Drip uses a special formulation that prevents dripping from your nose and down your throat.

How to use:

Push down cap while turning counter-clockwise and remove cap. Remove clip under rim. Secure cap after use.

TAMPER EVIDENT: DO NOT USE IF PRINTED SEAL OVER CAP IS BROKEN OR MISSING

IMPORTANT: Keep this carton for future reference on full labeling.

DISTRIBUTED BY:

WINCO FOODS LLC,

BOISE,ID 83704

*This product is not manufactured and distributed by Bayer distributor of Afrin®No Drip Extra Moisturizing

The Supermarket Low Price Leader®

100% Satisfaction Guarantee

Comments & Questions?

800-824-1706.www.wincofoods.com